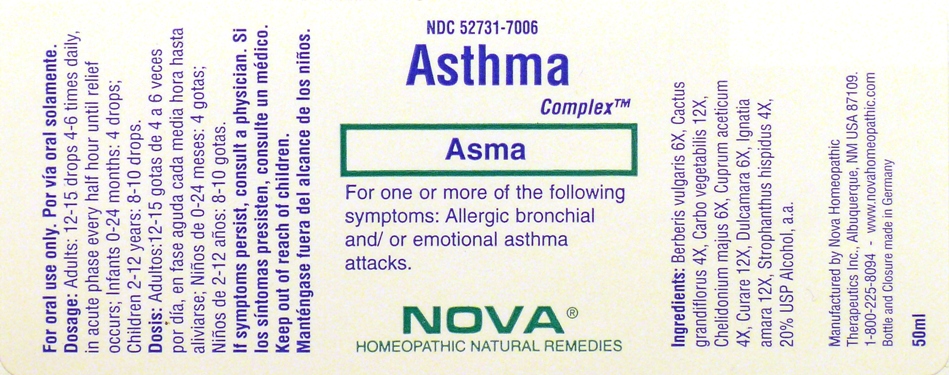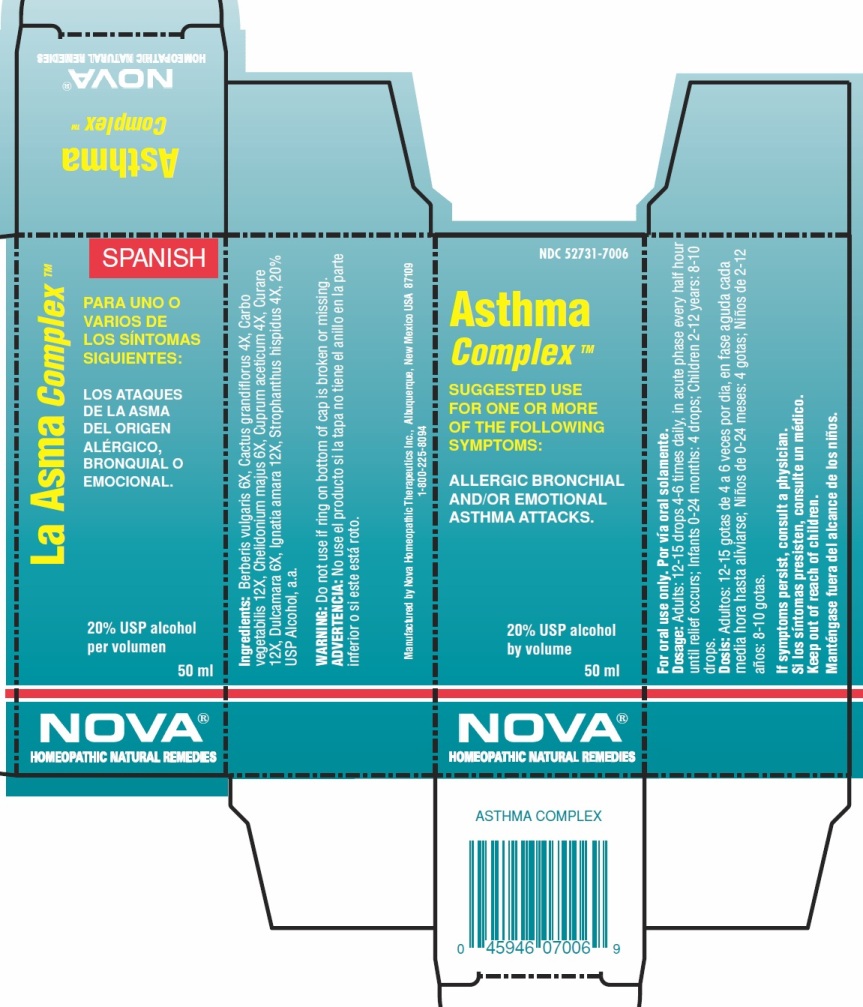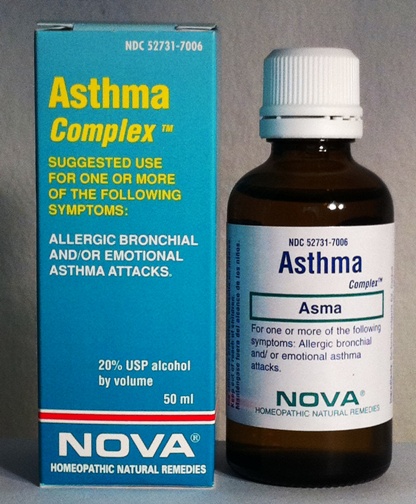 DRUG LABEL: Asthma Complex
NDC: 52731-7006 | Form: LIQUID
Manufacturer: Nova Homeopathic Therapeutics, Inc.
Category: homeopathic | Type: HUMAN OTC DRUG LABEL
Date: 20110601

ACTIVE INGREDIENTS: BERBERIS VULGARIS FRUIT 6 [hp_X]/1 mL; SELENICEREUS GRANDIFLORUS FLOWER 4 [hp_X]/1 mL; ACTIVATED CHARCOAL 12 [hp_X]/1 mL; CHELIDONIUM MAJUS 6 [hp_X]/1 mL; CUPRIC ACETATE 4 [hp_X]/1 mL; TUBOCURARINE CHLORIDE 12 [hp_X]/1 mL; SOLANUM DULCAMARA TOP 6 [hp_X]/1 mL; STRYCHNOS IGNATII SEED 12 [hp_X]/1 mL; STROPHANTHUS HISPIDUS SEED 4 [hp_X]/1 mL
INACTIVE INGREDIENTS: ALCOHOL

Content of Labeling

Purpose:

Suggested use for one or more of the following symptoms:
Allergic bronchial and/or emotional asthma attacks.

Usage & Dosage:

For oral use only.

DOSAGE AND ADMINISTRATION

Adults | 12-15 drops | 4-6 times daily, in accute phase every half hour until relief occurs
Children 2-12 years | 8-10 drops
Infants 0-24 months | 4 drops

Warnings:

Keep out of reach of children.

WARNINGS

If symptoms persist, consult a physician.

Do not use if ring on bottom of cap is broken or missing.

Active Ingredients:

Berberis vulgaris 6X, Cactus grandiflorus 4X, Carbo vegetabilis 12X, Chelidonium majus 6X, Cuprum aceticum 4X, Curare 12X, Dulcamara 6X, Ignatia amara 12X, Strophanthus hispidus 4X

Inactive Ingredients:

Alcohol, 20% USP

QUESTIONS

Manufactured by Nova Homeopathic Therapeutics Inc., Albuquerque, New Mexico USA 87109
1-800-225-8094

PACKAGE LABEL

Nova Asthma Complex Product
Nova Asthma Complex Bottle Label
Nova Asthma Complex Box